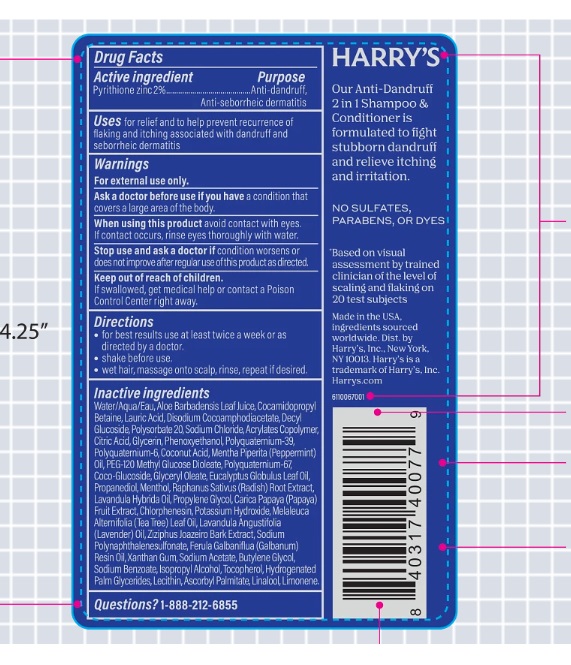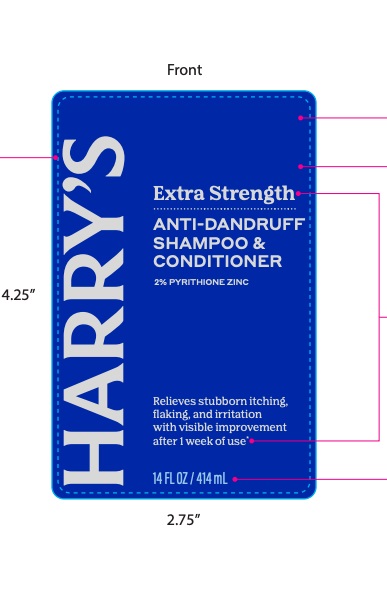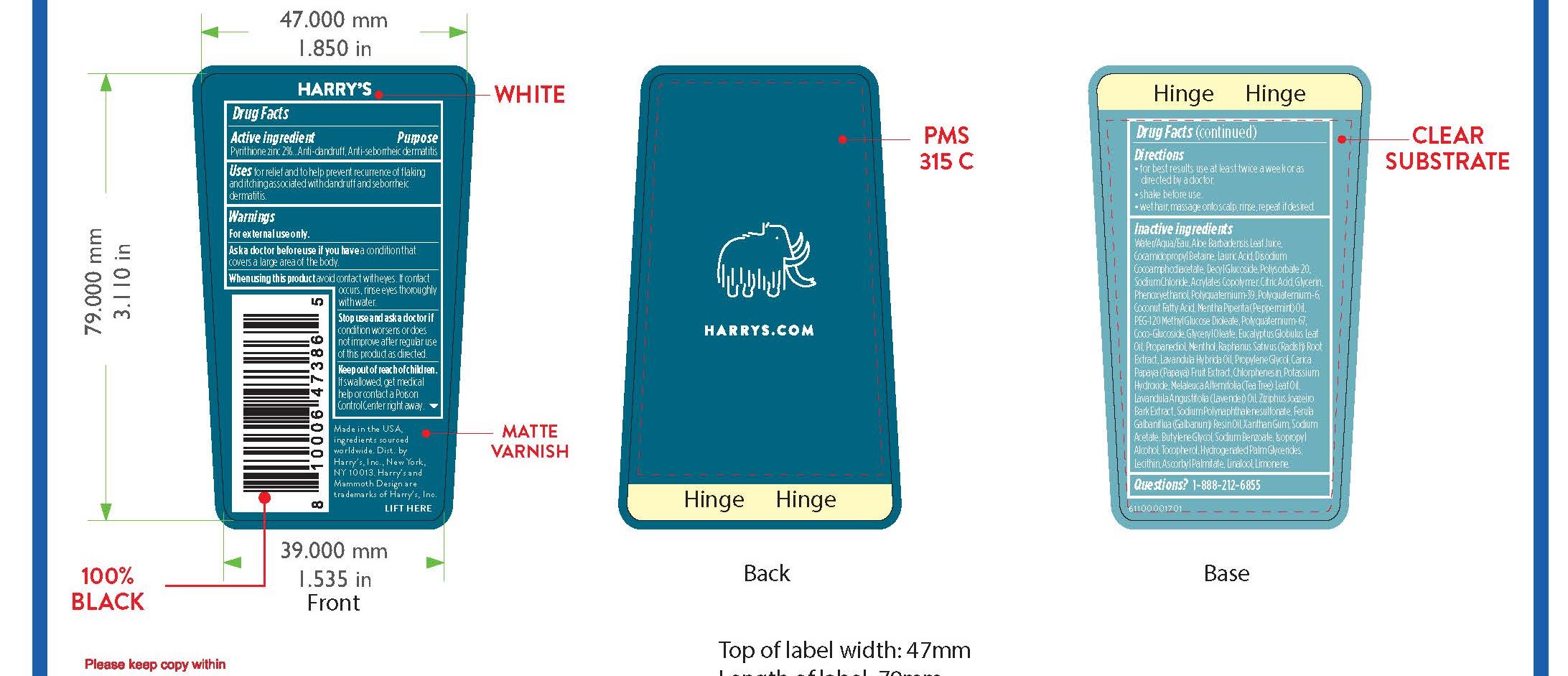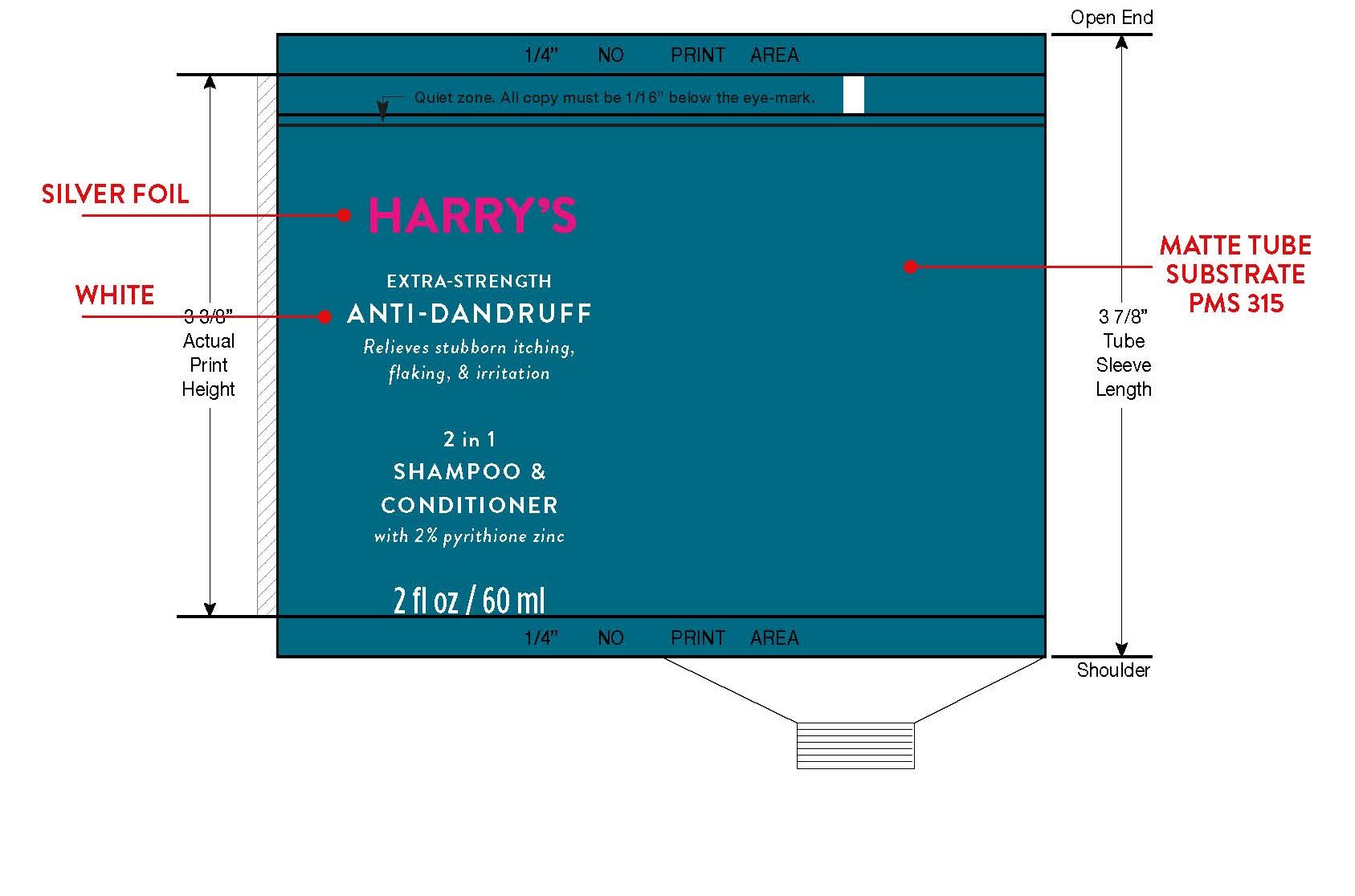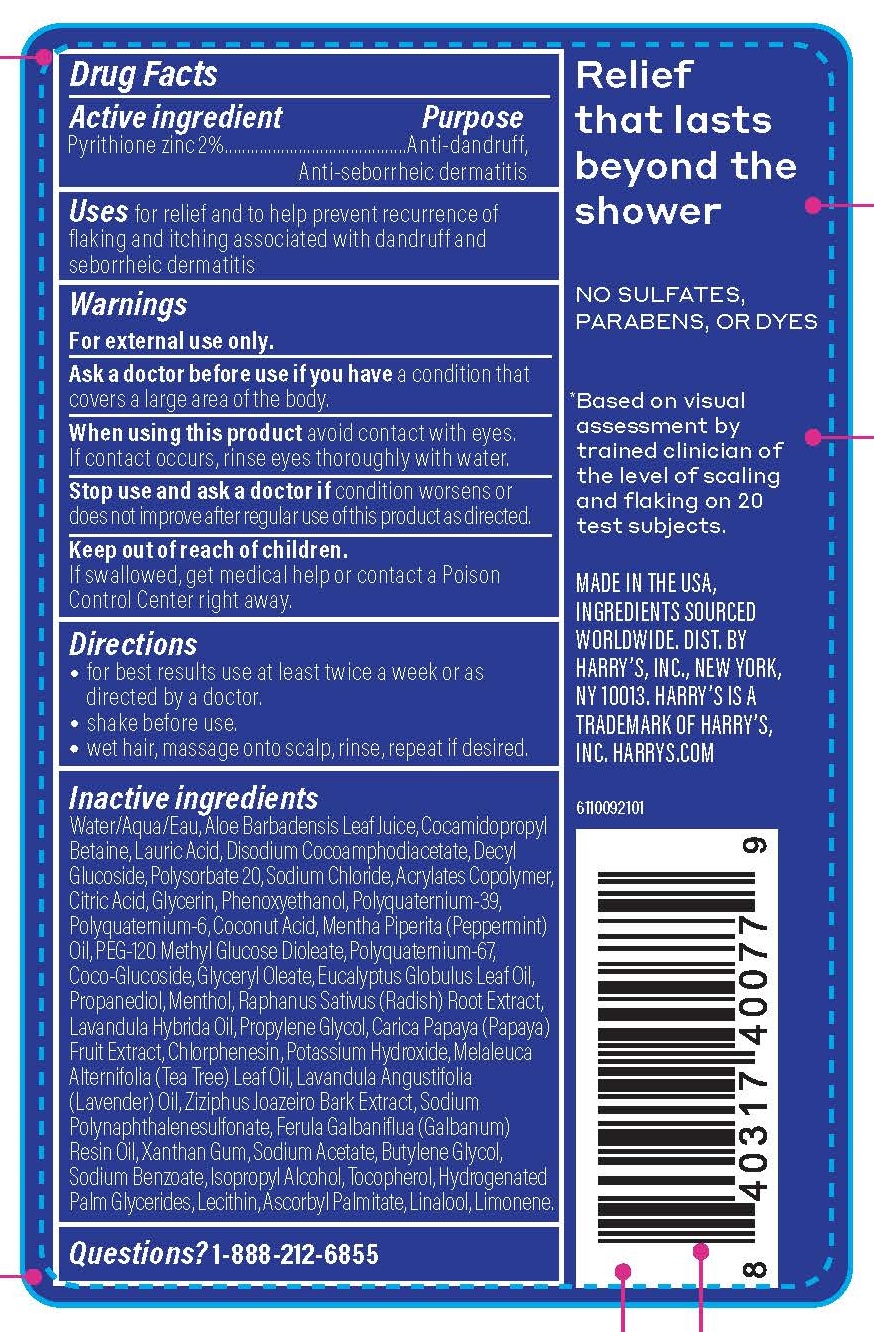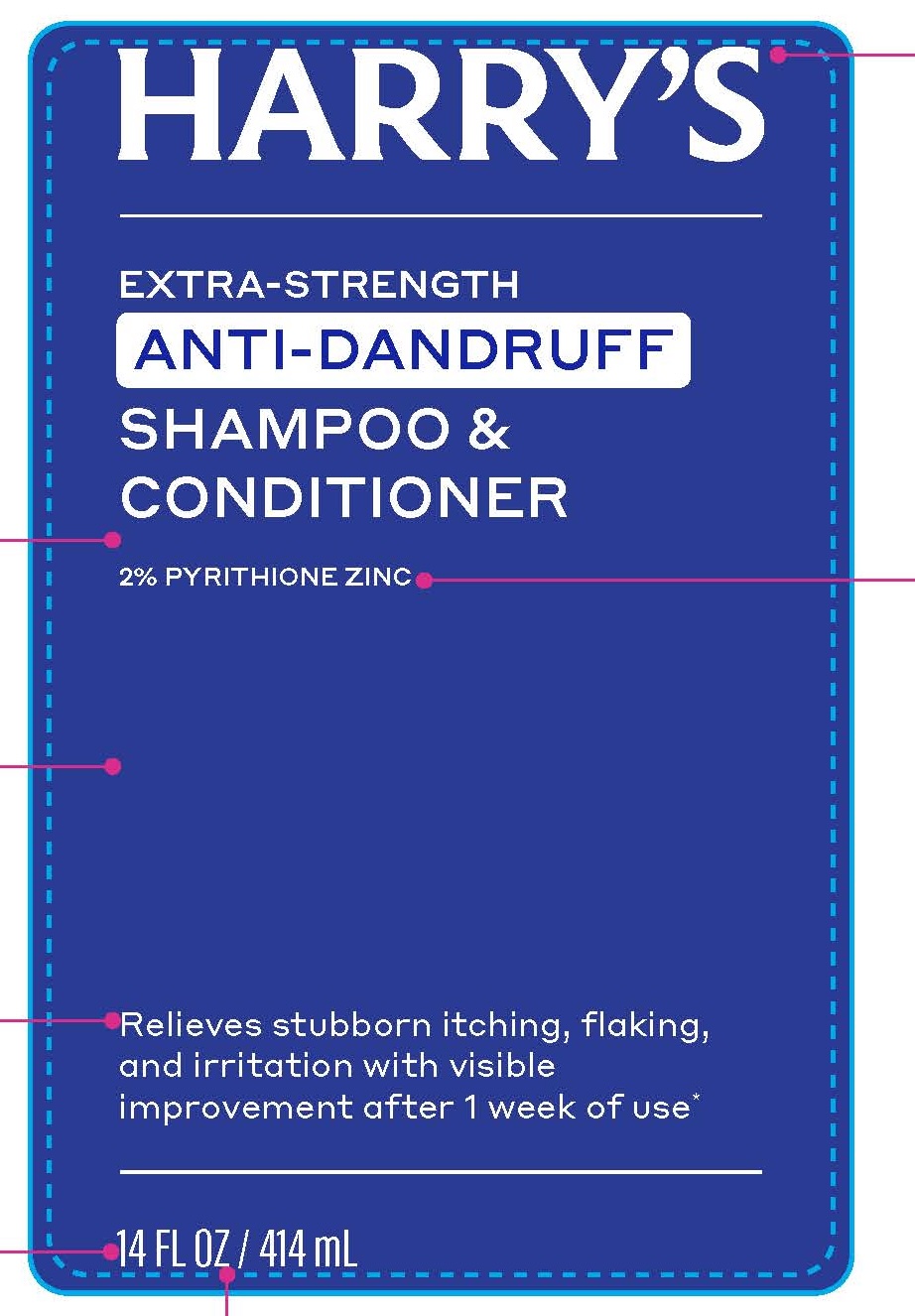 DRUG LABEL: Zinc Pyrithione
NDC: 70533-004 | Form: SHAMPOO
Manufacturer: Harry's Inc.
Category: otc | Type: HUMAN OTC DRUG LABEL
Date: 20251208

ACTIVE INGREDIENTS: PYRITHIONE ZINC 20 mg/2 mL
INACTIVE INGREDIENTS: RAPHANUS SATIVUS VAR. CAUDATUS ROOT; COCO GLUCOSIDE; LAVANDIN OIL; GUAR HYDROXYPROPYLTRIMONIUM CHLORIDE (1.7 SUBSTITUENTS PER SACCHARIDE); POLYQUATERNIUM-10 (400 CPS AT 2%); COCAMIDOPROPYL BETAINE; LAURIC ACID; CHLORPHENESIN; XANTHAN GUM; BENZOIC ACID; HYDROGENATED PALM GLYCERIDES; DISODIUM COCOAMPHODIACETATE; PEPPERMINT OIL; ASCORBYL PALMITATE; LAVENDER OIL; POLYSORBATE 20; WHITE PEPPER; COCONUT ACID; SODIUM CAPROYL LACTYLATE; TOCOPHEROL; PEG-120 METHYL GLUCOSE DIOLEATE; GLYCERIN; DECYL GLUCOSIDE; POLYQUATERNIUM-6 (15000 MW); SODIUM ACETATE ANHYDROUS; PROPYLENE GLYCOL; FORMALDEHYDE/SODIUM NAPHTHALENESULFONATE COPOLYMER (3000 MW); ALOE; INGA ALBA BARK; LECITHIN, SUNFLOWER; SODIUM CHLORIDE; ANHYDROUS CITRIC ACID; RACEMENTHOL; GLYCERYL OLEATE; LIMONENE, (+/-)-; ISOPROPYL ALCOHOL; WATER; SODIUM LAUROYL LACTYLATE; GALBANUM OIL; POTASSIUM HYDROXIDE; TEA TREE OIL; BUTYLENE GLYCOL; PHENOXYETHANOL; PAPAYA; DEHYDROACETIC ACID; METHACRYLIC ACID - ETHYL ACRYLATE COPOLYMER (4500 MPA.S); EUCALYPTUS OIL; LINALOOL, (+/-)-

Anti-dandruff - Extra Strengtth

Active Ingredients

Zinc Pyrithione 2%

Purpose

Anti-dandruff,

Ant-seborrheic dermatitis

Uses

for relief and to help prevent recurrence of flaking and itching associated with dandruff and seborrheic dermatitis.

Warnings

For external use only.

Ask a doctor before use if you have a condition that covers a large area of the body.

When using this product avoid contact with eyes. If contact occurs, rinse eyes thoroughly with water.

Stop use and ask a doctor if condition worsens or does not improve after regular use of this product as directed.

Keep out of reach of children. If swallowed, get medical help or contact a Poison Control Center right away.

Directions

• for best results use at least twice a week or as
directed by a doctor.
• shake before use.
• wet hair, massage onto scalp, rinse, repeat if desired.

Inactive ingredients

Water/Aqua/Eau, Aloe Barbadensis Leaf Juice,Cocamidopropyl Betaine, Lauric Acid, Disodium Cocoamphodiacetate, Decyl Glucoside, Polysorbate 20, Sodium Chloride, Acrylates Copolymer, Citric Acid, Glycerin, Phenoxyethanol, Polyquaternium-39, Polyquaternium-6, Coconut Acid, Mentha Piperita (Peppermint) Oil, PEG-120 Methyl Glucose Dioleate, Polyquaternium-67, Coco-Glucoside, Glyceryl Oleate, Eucalyptus Globulus Leaf Oil, Propanediol, Menthol, Raphanus Sativus (Radish) Root Extract, Lavandula Hybrida Oil, Propylene Glycol, Carica Papaya (Papaya) Fruit Extract, Chlorphenesin, Potassium Hydroxide, Melaleuca Alternifolia (Tea Tree) Leaf Oil, Lavandula Angustifolia (Lavender) Oil, Ziziphus Joazeiro Bark Extract, Sodium Polynaphthalenesulfonate, Ferula Galbaniflua (Galbanum) Resin Oil, Xanthan Gum, Sodium Acetate, Butylene Glycol, Sodium Benzoate, Isopropyl Alcohol, Tocopherol, Hydrogenated Palm Glycerides, Lecithin, Ascorbyl Palmitate, Linalool, Limonene.

Questions? 1-888-212-6855

PACKAGE LABEL

414 mL NDC: 70533-004-14

60 mL NDC: 70533-004-02